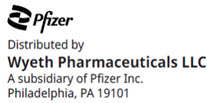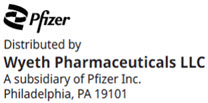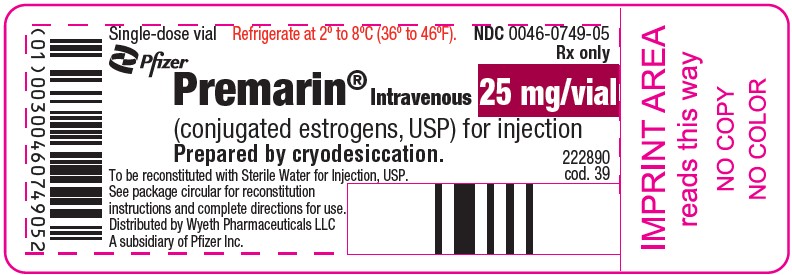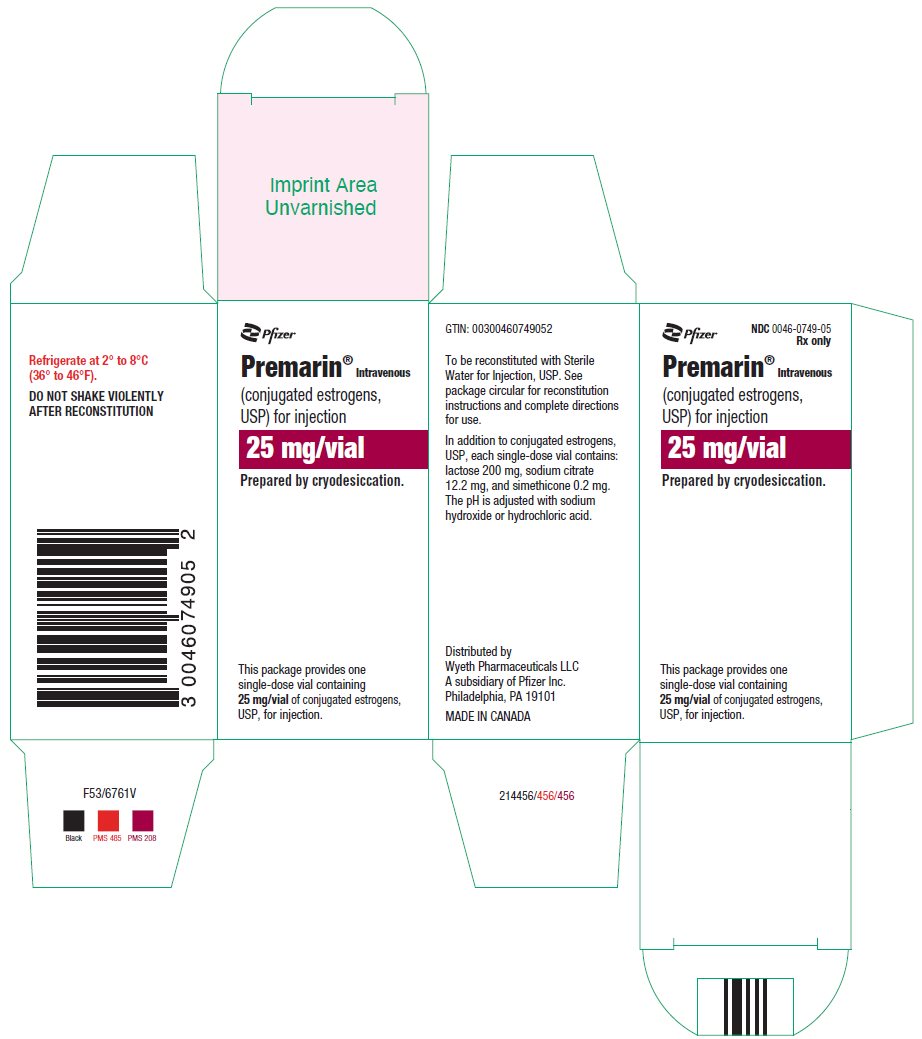 DRUG LABEL: Premarin
NDC: 0046-0749 | Form: INJECTION, POWDER, LYOPHILIZED, FOR SOLUTION
Manufacturer: Wyeth Pharmaceuticals LLC, a subsidiary of Pfizer Inc.
Category: prescription | Type: HUMAN PRESCRIPTION DRUG LABEL
Date: 20250530

ACTIVE INGREDIENTS: ESTROGENS, CONJUGATED 25 mg/5 mL
INACTIVE INGREDIENTS: LACTOSE MONOHYDRATE 200 mg/5 mL; SODIUM CITRATE, UNSPECIFIED FORM 12.2 mg/5 mL

Premarin®
Intravenous
(conjugated estrogens, USP) for injection

Specially prepared for Intravenous & Intramuscular use

Rx only

WARNING: ENDOMETRIAL CANCER, CARDIOVASCULAR DISORDERS, BREAST CANCER and PROBABLE DEMENTIA

Estrogen-Alone Therapy

Endometrial Cancer

There is an increased risk of endometrial cancer in a woman with a uterus who uses unopposed estrogens. Adding a progestin to estrogen therapy has been shown to reduce the risk of endometrial hyperplasia, which may be a precursor to endometrial cancer. Adequate diagnostic measures, including directed or random endometrial sampling when indicated, should be undertaken to rule out malignancy in postmenopausal women with undiagnosed persistent or recurring abnormal genital bleeding. (See WARNINGS, Malignant Neoplasms, Endometrial cancer.)

Cardiovascular Disorders and Probable Dementia

Estrogen-alone therapy should not be used for the prevention of cardiovascular disease or dementia. (See CLINICAL STUDIES and WARNINGS, Cardiovascular Disorders and Probable Dementia.)

The Women's Health Initiative (WHI) estrogen-alone substudy reported increased risks of stroke and deep vein thrombosis (DVT) in postmenopausal women (50 to 79 years of age) during 7.1 years of treatment with daily oral conjugated estrogens (CE) [0.625 mg]-alone, relative to placebo. (See CLINICAL STUDIES and WARNINGS, Cardiovascular disorders.)

The WHI Memory Study (WHIMS) estrogen-alone ancillary study of the WHI reported an increased risk of developing probable dementia in postmenopausal women 65 years of age or older during 5.2 years of treatment with daily CE (0.625 mg)-alone, relative to placebo. It is unknown whether this finding applies to younger postmenopausal women. (See CLINICAL STUDIES and WARNINGS, Probable Dementia and PRECAUTIONS, Geriatric Use.)

In the absence of comparable data, these risks should be assumed to be similar for other doses of CE and other dosage forms of estrogens.

Estrogens with or without progestins should be prescribed at the lowest effective doses and for the shortest duration consistent with treatment goals and risks for the individual woman.

Estrogen Plus Progestin Therapy

Cardiovascular Disorders and Probable Dementia

Estrogen plus progestin therapy should not be used for the prevention of cardiovascular disease or dementia. (See CLINICAL STUDIES and WARNINGS, Cardiovascular disorders and Probable Dementia.)

The WHI estrogen plus progestin substudy reported increased risks of DVT, pulmonary embolism (PE), stroke and myocardial infarction (MI) in postmenopausal women (50 to 79 years of age) during 5.6 years of treatment with daily oral CE (0.625 mg) combined with medroxyprogesterone acetate (MPA) [2.5 mg], relative to placebo. (See CLINICAL STUDIES and WARNINGS, Cardiovascular disorders.)

The WHIMS estrogen plus progestin ancillary study of the WHI reported an increased risk of developing probable dementia in postmenopausal women 65 years of age or older during 4 years of treatment with daily CE (0.625 mg) combined with MPA (2.5 mg), relative to placebo. It is unknown whether this finding applies to younger postmenopausal women. (See CLINICAL STUDIES and WARNINGS, Probable Dementia and PRECAUTIONS, Geriatric Use.)

Breast Cancer

The WHI estrogen plus progestin substudy also demonstrated an increased risk of invasive breast cancer. (See CLINICAL STUDIES and WARNINGS, Malignant Neoplasms, Breast cancer.)

In the absence of comparable data, these risks should be assumed to be similar for other doses of CE and MPA, and other combinations and dosage forms of estrogens and progestins.

Estrogens with or without progestins should be prescribed at the lowest effective doses and for the shortest duration consistent with treatment goals and risks for the individual woman.

DESCRIPTION

Premarin Intravenous (conjugated estrogens, USP) for injection contains a mixture of conjugated estrogens obtained exclusively from natural sources, occurring as the sodium salts of water-soluble estrogen sulfates blended to represent the average composition of materials derived from pregnant mares' urine. It is a mixture of sodium estrone sulfate and sodium equilin sulfate. It contains as concomitant components, as sodium sulfate conjugates, 17α-dihydroequilin, 17α-estradiol, and 17β-dihydroequilin.

Each single-dose vial contains 25 mg/vial of conjugated estrogens, USP, in a sterile lyophilized cake which also contains lactose 200 mg, sodium citrate 12.2 mg, and simethicone 0.2 mg. The pH is adjusted with sodium hydroxide or hydrochloric acid. The reconstituted solution is suitable for intravenous or intramuscular injection.

CLINICAL PHARMACOLOGY

Endogenous estrogens are largely responsible for the development and maintenance of the female reproductive system and secondary sexual characteristics. Although circulating estrogens exist in a dynamic equilibrium of metabolic interconversions, estradiol is the principal intracellular human estrogen and is substantially more potent than its metabolites, estrone and estriol, at the receptor level. The primary source of estrogen in normally cycling adult women is the ovarian follicle, which secretes 70 to 500 mcg of estradiol daily, depending on the phase of the menstrual cycle. After menopause, most endogenous estrogen is produced by conversion of androstenedione, secreted by the adrenal cortex, to estrone in the peripheral tissues. Thus, estrone and the sulfate-conjugated form, estrone sulfate, are the most abundant circulating estrogen in postmenopausal women.

Estrogens act through binding to nuclear receptors in estrogen-responsive tissues. To date, two estrogen receptors have been identified. These vary in proportion from tissue to tissue.

Circulating estrogens modulate the pituitary secretion of the gonadotropins, luteinizing hormone (LH) and follicle stimulating hormone (FSH), through a negative feedback mechanism. Estrogens act to reduce the elevated levels of these gonadotropins seen in postmenopausal women.

Pharmacokinetics

A. Absorption

Conjugated estrogens are water-soluble and are well-absorbed through the skin, mucous membranes, and gastrointestinal tract after release from the drug formulation.

B. Distribution

The distribution of exogenous estrogens is similar to that of endogenous estrogens. Estrogens are widely distributed in the body and are generally found in higher concentration in the sex hormone target organs. Estrogens circulate in the blood largely bound to sex hormone-binding globulin (SHBG) and albumin.

C. Metabolism

Exogenous estrogens are metabolized in the same manner as endogenous estrogens. Circulating estrogens exist in a dynamic equilibrium of metabolic interconversions. These transformations take place mainly in the liver. Estradiol is converted reversibly to estrone, and both can be converted to estriol, which is a major urinary metabolite. Estrogens also undergo enterohepatic recirculation via sulfate and glucuronide conjugation in the liver, biliary secretion of conjugates into the intestine, and hydrolysis in the intestine followed by reabsorption. In postmenopausal women a significant proportion of the circulating estrogens exist as sulfate conjugates, especially estrone sulfate, which serves as a circulating reservoir for the formation of more active estrogens.

D. Excretion

Estradiol, estrone, and estriol are excreted in the urine along with glucuronide and sulfate conjugates.

E. Special Populations

No pharmacokinetic studies were conducted in special populations, including patients with renal or hepatic impairment.

F. Drug Interactions

Data from a single-dose drug-drug interaction study involving oral CE and MPA indicate that the pharmacokinetic dispositions of both drugs are not altered when the drugs are coadministered. No other clinical drug-drug interaction studies have been conducted with conjugated estrogens.

In vitro and in vivo studies have shown that estrogens are metabolized partially by cytochrome P450 3A4 (CYP3A4). Therefore, inducers or inhibitors of CYP3A4 may affect estrogen drug metabolism. Inducers of CYP3A4, such as St. John's wort (Hypericum perforatum) preparations, phenobarbital, carbamazepine, and rifampin, may reduce plasma concentrations of estrogens, possibly resulting in a decrease in therapeutic effects and/or changes in the uterine bleeding profile. Inhibitors of CYP3A4, such as erythromycin, clarithromycin, ketoconazole, itraconazole, ritonavir and grapefruit juice, may increase plasma concentrations of estrogens and may result in side effects.

CLINICAL STUDIES

Women's Health Initiative Studies

The Women's Health Initiative (WHI) enrolled approximately 27,000 predominantly healthy postmenopausal women in two substudies to assess the risks and benefits of daily oral CE (0.625 mg)-alone or in combination with MPA (2.5 mg) compared to placebo in the prevention of certain chronic diseases. The primary endpoint was the incidence of coronary heart disease [(CHD) defined as nonfatal MI, silent MI and CHD death], with invasive breast cancer as the primary adverse outcome. A "global index" included the earliest occurrence of CHD, invasive breast cancer, stroke, PE, endometrial cancer (only in CE plus MPA substudy), colorectal cancer, hip fracture, or death due to other causes. These studies did not evaluate the effects of CE-alone or CE plus MPA on menopausal symptoms.

WHI Estrogen-Alone Substudy

The WHI estrogen-alone substudy was stopped early because an increased risk of stroke was observed, and it was deemed that no further information would be obtained regarding the risks and benefits of estrogen-alone in predetermined primary endpoints.

Results of the estrogen-alone substudy, which included 10,739 women (average 63 years of age, range 50 to 79; 75.3 percent White, 15.1 percent Black, 6.1 percent Hispanic, 3.6 percent Other) after an average follow-up of 7.1 years, are presented in Table 1.

TABLE 1. RELATIVE AND ABSOLUTE RISK SEEN IN THE ESTROGEN-ALONE SUBSTUDY OF WHI [Adapted from numerous WHI publications. WHI publications can be viewed at www.nhlbi.nih.gov/whi.]
Event | Relative Risk CE vs. Placebo (95% nCI [Nominal confidence intervals unadjusted for multiple looks and multiple comparisons.]) | CE n = 5,310 | Placebo n = 5,429
Event | Relative Risk CE vs. Placebo (95% nCI [Nominal confidence intervals unadjusted for multiple looks and multiple comparisons.]) | Absolute Risk per 10,000 Women-Years
CHD events [Results are based on centrally adjudicated data for an average follow-up of 7.1 years.] | 0.95 (0.78–1.16) | 54 | 57
Non-fatal MI | 0.91 (0.73–1.14) | 40 | 43
CHD death | 1.01 (0.71–1.43) | 16 | 16
All Stroke | 1.33 (1.05–1.68) | 45 | 33
Ischemic stroke | 1.55 (1.19–2.01) | 38 | 25
Deep vein thrombosis, [Not included in Global Index.] | 1.47 (1.06–2.06) | 23 | 15
Pulmonary embolism | 1.37 (0.90–2.07) | 14 | 10
Invasive breast cancer | 0.80 (0.62–1.04) | 28 | 34
Colorectal cancer [Results are based on an average follow-up of 6.8 years.] | 1.08 (0.75–1.55) | 17 | 16
Hip fracture | 0.65 (0.45–0.94) | 12 | 19
Vertebral fractures, | 0.64 (0.44–0.93) | 11 | 18
Lower arm/wrist fractures, | 0.58 (0.47–0.72) | 35 | 59
Total fractures, | 0.71 (0.64–0.80) | 144 | 197
Death due to other causes, [All deaths, except from breast or colorectal cancer, definite or probable CHD, PE or cerebrovascular disease.] | 1.08 (0.88–1.32) | 53 | 50
Overall mortality, | 1.04 (0.88–1.22) | 79 | 75
Global Index [A subset of the events was combined in a "global index," defined as the earliest occurrence of CHD events, invasive breast cancer, stroke, pulmonary embolism, colorectal cancer, hip fracture, or death due to other causes.] | 1.02 (0.92–1.13) | 206 | 201

For those outcomes included in the WHI "global index" that reached statistical significance, the absolute excess risk per 10,000 women-years in the group treated with CE-alone were 12 more strokes, while the absolute risk reduction per 10,000 women-years was 7 fewer hip fractures. The absolute excess risk of events included in the "global index" was a nonsignificant 5 events per 10,000 women-years. There was no difference between the groups in terms of all-cause mortality.

No overall difference for primary CHD events (nonfatal MI, silent MI and CHD death) and invasive breast cancer incidence in women receiving CE-alone compared with placebo was reported in final centrally adjudicated results from the estrogen-alone substudy, after an average follow-up of 7.1 years.

Centrally adjudicated results for stroke events from the estrogen-alone substudy, after an average follow-up of 7.1 years, reported no significant difference in distribution of stroke subtype or severity, including fatal strokes, in women receiving CE-alone compared to placebo. Estrogen alone increased the risk of ischemic stroke, and this excess was present in all subgroups of women examined.

Timing of the initiation of estrogen-alone therapy relative to the start of menopause may affect the overall risk benefit profile. The WHI estrogen-alone substudy stratified by age showed in women 50 to 59 years of age, a non-significant trend toward reduced risk for CHD [hazard ratio (HR) 0.63 (95 percent CI, 0.36–1.09)] and overall mortality [HR 0.71 (95 percent CI, 0.46–1.11)].

WHI Estrogen Plus Progestin Substudy

The WHI estrogen plus progestin substudy was stopped early. According to the predefined stopping rule, after an average follow-up of 5.6 years of treatment, the increased risk of invasive breast cancer and cardiovascular events exceeded the specified benefits included in the "global index." The absolute excess risk of events included in the "global index" was 19 per 10,000 women-years.

For those outcomes included in the WHI "global index" that reached statistical significance after 5.6 years of follow-up, the absolute excess risks per 10,000 women-years in the group treated with CE plus MPA were 7 more CHD events, 8 more strokes, 10 more PEs, and 8 more invasive breast cancers, while the absolute risk reductions per 10,000 women-years were 6 fewer colorectal cancers and 5 fewer hip fractures. Results of the estrogen plus progestin substudy, which included 16,608 women (average 63 years of age, range 50 to 79; 83.9 percent White, 6.8 percent Black, 5.4 percent Hispanic, 3.9 percent Other) are presented in Table 2. These results reflect centrally adjudicated data after an average follow-up of 5.6 years.

TABLE 2. RELATIVE AND ABSOLUTE RISK SEEN IN THE ESTROGEN PLUS PROGESTIN SUBSTUDY OF WHI AT AN AVERAGE OF 5.6 YEARS [Adapted from numerous WHI publications. WHI publications can be viewed at www.nhlbi.nih.gov/whi.] , [Results are based on centrally adjudicated data.]
Event | Relative Risk CE/MPA vs. Placebo (95% nCI [Nominal confidence intervals unadjusted for multiple looks and multiple comparisons.]) | CE/MPA n = 8,506 | Placebo n = 8,102
Event | Relative Risk CE/MPA vs. Placebo (95% nCI [Nominal confidence intervals unadjusted for multiple looks and multiple comparisons.]) | Absolute Risk per 10,000 Women-Years
CHD events | 1.23 (0.99–1.53) | 41 | 34
Non-fatal MI | 1.28 (1.00–1.63) | 31 | 25
CHD death | 1.10 (0.70–1.75) | 8 | 8
All Strokes | 1.31 (1.03–1.68) | 33 | 25
Ischemic Stroke | 1.44 (1.09–1.90) | 26 | 18
Deep vein thrombosis [Not included in "global index".] | 1.95 (1.43–2.67) | 26 | 13
Pulmonary embolism | 2.13 (1.45–3.11) | 18 | 8
Invasive breast cancer [Includes metastatic and non-metastatic breast cancer, with the exception of in situ breast cancer.] | 1.24 (1.01–1.54) | 41 | 33
Colorectal cancer | 0.61 (0.42–0.87) | 10 | 16
Endometrial cancer | 0.81 (0.48–1.36) | 6 | 7
Cervical cancer | 1.44 (0.47–4.42) | 2 | 1
Hip fracture | 0.67 (0.47–0.96) | 11 | 16
Vertebral fractures | 0.65 (0.46–0.92) | 11 | 17
Lower arm/wrist fractures | 0.71 (0.59–0.85) | 44 | 62
Total fractures | 0.76 (0.69–0.83) | 152 | 199
Overall mortality [All deaths, except from breast or colorectal cancer, definite or probable CHD, PE or cerebrovascular disease.] | 1.00 (0.83–1.19) | 52 | 52
Global Index [A subset of the events was combined in a "global index," defined as the earliest occurrence of CHD events, invasive breast cancer, stroke, pulmonary embolism, colorectal cancer, hip fracture, or death due to other causes.] | 1.13 (1.02–1.25) | 184 | 165

Timing of the initiation of estrogen plus progestin therapy relative to the start of menopause may affect the overall risk benefit profile. The WHI estrogen plus progestin substudy stratified by age showed in women 50 to 59 years of age a non-significant trend toward reduced risk for overall mortality [HR 0.69 (95 percent CI, 0.44–1.07)].

Women's Health Initiative Memory Study

The WHIMS estrogen-alone ancillary study of WHI enrolled 2,947 predominantly healthy postmenopausal women 65 to 79 years of age and older (45 percent were 65 to 69 years of age; 36 percent were 70 to 74 years of age; 19 percent were 75 years of age and older) to evaluate the effects of daily CE (0.625 mg)-alone on the incidence of probable dementia (primary outcome) compared to placebo.

After an average follow-up of 5.2 years, the relative risk of probable dementia for CE-alone versus placebo was 1.49 (95 percent CI, 0.83–2.66). The absolute risk of probable dementia for CE-alone versus placebo was 37 versus 25 cases per 10,000 women-years. Probable dementia as defined in this study included Alzheimer disease (AD), vascular dementia (VaD) and mixed type (having features of both AD and VaD). The most common classification of probable dementia in the treatment group and the placebo group was AD. Since the ancillary study was conducted in women 65 to 79 years of age, it is unknown whether these findings apply to younger postmenopausal women. (See WARNINGS, Probable Dementia and PRECAUTIONS, Geriatric Use.)

The WHIMS estrogen plus progestin ancillary study enrolled 4,532 predominantly healthy postmenopausal women 65 years of age and older (47 percent were 65 to 69 years of age; 35 percent were 70 to 74 years of age; 18 percent were 75 years of age and older) to evaluate the effects of daily CE (0.625 mg) plus MPA (2.5 mg) on the incidence of probable dementia (primary outcome) compared to placebo.

After an average follow-up of 4 years, the relative risk of probable dementia for CE plus MPA was 2.05 (95 percent CI, 1.21–3.48). The absolute risk of probable dementia for CE plus MPA versus placebo was 45 versus 22 per 10,000 women-years. Probable dementia as defined in this study included AD, VaD and mixed type (having features of both AD and VaD). The most common classification of probable dementia in the treatment group and the placebo group was AD. Since the ancillary study was conducted in women 65 to 79 years of age, it is unknown whether these findings apply to younger postmenopausal women. (See WARNINGS, Probable Dementia and PRECAUTIONS, Geriatric Use.)

When data from the two populations were pooled as planned in the WHIMS protocol, the reported overall relative risk for probable dementia was 1.76 (95 percent CI, 1.19–2.60). Differences between groups became apparent in the first year of treatment. It is unknown whether these findings apply to younger postmenopausal women. (See WARNINGS, Probable Dementia and PRECAUTIONS, Geriatric Use.)

INDICATIONS AND USAGE

Premarin Intravenous (conjugated estrogens, USP) for injection is indicated in the treatment of abnormal uterine bleeding due to hormonal imbalance in the absence of organic pathology.

Premarin Intravenous is indicated for short-term use only, to provide a rapid and temporary increase in estrogen levels.

CONTRAINDICATIONS

Premarin Intravenous therapy should not be used in individuals with any of the following conditions:

1. Undiagnosed abnormal genital bleeding.
2. Known, suspected, or history of breast cancer.
3. Known or suspected estrogen-dependent neoplasia.
4. Active DVT, PE or a history of these conditions.
5. Active arterial thromboembolic disease (for example, stroke and MI) or a history of these conditions.
6. Known anaphylactic reaction and angioedema to Premarin Intravenous therapy.
7. Known liver dysfunction or disease.
8. Known protein C, protein S, or antithrombin deficiency or other known thrombophilic disorders.
9. Known or suspected pregnancy.

WARNINGS

See BOXED WARNINGS.

Premarin Intravenous for injection is indicated for short-term use. However, warnings, precautions and adverse reactions associated with oral Premarin treatment should be taken into account.

1. Cardiovascular Disorders

An increased risk of stroke and DVT has been reported with estrogen-alone therapy.

An increased risk of PE, DVT, stroke, and MI has been reported with estrogen plus progestin therapy.

Should any of these events occur or be suspected, estrogen with or without progestin therapy should be discontinued immediately.

Risk factors for arterial vascular disease (for example, hypertension, diabetes mellitus, tobacco use, hypercholesterolemia, and obesity) and/or venous thromboembolism (VTE) (for example, personal history or family history of VTE, obesity, and systemic lupus erythematosus) should be managed appropriately.

a. Stroke

In the WHI estrogen-alone substudy, a statistically significant increased risk of stroke was reported in women 50 to 79 years of age receiving daily CE (0.625 mg)-alone compared to women in the same age group receiving placebo (45 versus 33 per 10,000 women-years). (See CLINICAL STUDIES.) The increase in risk was demonstrated in year 1 and persisted. Should a stroke occur or be suspected, estrogen-alone therapy should be discontinued immediately.

Subgroup analyses of women 50 to 59 years of age suggest no increased risk of stroke for those women receiving CE (0.625 mg)-alone versus those receiving placebo (18 versus 21 per 10,000 women-years).

In the WHI estrogen plus progestin substudy, a statistically significant increased risk of stroke was reported in women 50 to 79 years of age receiving daily CE (0.625 mg) plus MPA (2.5 mg) compared to women in the same age group receiving placebo (33 versus 25 per 10,000 women-years). (See CLINICAL STUDIES.) The increase in risk was demonstrated after the first year and persisted. Should a stroke occur or be suspected, estrogen plus progestin therapy should be discontinued immediately.

b. Coronary heart disease

In the WHI estrogen-alone substudy, no overall effect on CHD events (defined as nonfatal MI, silent MI, or CHD death) was reported in women receiving estrogen-alone compared to placebo. (See CLINICAL STUDIES.)

In the WHI estrogen plus progestin substudy, there was a non-statistically significant increased risk of CHD events reported in women receiving daily CE (0.625 mg) plus MPA (2.5 mg) compared to women receiving placebo (41 versus 34 per 10,000 women-years). An increase in relative risk was demonstrated in year 1, and a trend toward decreasing relative risk was reported in years 2 through 5.

In postmenopausal women with documented heart disease (n = 2,763, average 66.7 years of age), in a controlled clinical trial of secondary prevention of cardiovascular disease (Heart and Estrogen/Progestin Replacement Study; HERS), treatment with daily CE 0.625 mg/MPA 2.5 mg demonstrated no cardiovascular benefit. During an average follow-up of 4.1 years, treatment with CE plus MPA did not reduce the overall rate of CHD events in postmenopausal women with established coronary heart disease. There were more CHD events in the CE plus MPA-treated group than in the placebo group in year one, but not during the subsequent years. Two thousand three hundred and twenty-one (2,321) women from the original HERS trial agreed to participate in an open-label extension of HERS, HERS II. Average follow-up in HERS II was an additional 2.7 years, for a total of 6.8 years overall. Rates of CHD events were comparable among women in the CE plus MPA group and the placebo group in the HERS, the HERS II, and overall.

c. Venous thromboembolism

In the WHI estrogen-alone substudy, the risk of VTE (DVT and PE), was increased for women receiving daily CE (0.625 mg)-alone compared to placebo (30 versus 22 per 10,000 women-years), although only the increased risk of DVT reached statistical significance (23 versus 15 per 10,000 women-years). The increase in VTE risk was demonstrated during the first 2 years. (See CLINICAL STUDIES.) Should a VTE occur or be suspected, estrogen-alone therapy should be discontinued immediately.

In the WHI estrogen plus progestin substudy, a statistically significant 2-fold greater rate of VTE was reported in women receiving daily CE (0.625 mg) plus MPA (2.5 mg) compared to women receiving placebo (35 versus 17 per 10,000 women-years). Statistically significant increases in risk for both DVT (26 versus 13 per 10,000 women-years) and PE (18 versus 8 per 10,000 women-years) were also demonstrated. The increase in VTE risk was demonstrated during the first year and persisted. (See CLINICAL STUDIES.) Should a VTE occur or be suspected, estrogen plus progestin therapy should be discontinued immediately.

2. Malignant Neoplasms

a. Endometrial cancer

An increased risk of endometrial cancer has been reported with the use of unopposed estrogen therapy in women with a uterus. The reported endometrial cancer risk among unopposed estrogen users is about 2 to 12 times greater than in non-users, and appears dependent on duration of treatment and on estrogen dose. Most studies show no significant increased risk associated with use of estrogens for less than 1 year. The greatest risk appears associated with prolonged use, with increased risks of 15- to 24-fold for 5 to 10 years or more and this risk has been shown to persist for at least 8 to 15 years after estrogen therapy is discontinued.

b. Breast cancer

The WHI substudy of daily CE (0.625 mg)-alone provided information about breast cancer in estrogen-alone users. In the WHI estrogen-alone substudy, after an average follow-up of 7.1 years, daily CE (0.625 mg)-alone was not associated with an increased risk of invasive breast cancer (relative risk [RR] 0.80). (See CLINICAL STUDIES.)

After a mean follow-up of 5.6 years, the WHI substudy of daily CE (0.625 mg) plus MPA (2.5 mg) reported an increased risk of invasive breast cancer in women who took daily CE plus MPA compared to placebo. In this substudy, prior use of estrogen-alone or estrogen plus progestin therapy was reported by 26 percent of the women. The relative risk of invasive breast cancer was 1.24, and the absolute risk was 41 versus 33 cases per 10,000 women-years, for CE plus MPA compared with placebo. Among women who reported prior use of hormone therapy, the relative risk of invasive breast cancer was 1.86, and the absolute risk was 46 versus 25 cases per 10,000 women-years, for CE plus MPA compared with placebo. Among women who reported no prior use of hormone therapy, the relative risk of invasive breast cancer was 1.09, and the absolute risk was 40 versus 36 cases per 10,000 women-years for CE plus MPA compared with placebo. In the same substudy, invasive breast cancers were larger, were more likely to be node positive, and were diagnosed at a more advanced stage in the CE (0.625 mg) plus MPA (2.5 mg) group compared with the placebo group. Metastatic disease was rare, with no apparent difference between the two groups. Other prognostic factors, such as histologic subtype, grade and hormone receptor status did not differ between the groups. (See CLINICAL STUDIES.)

Consistent with the WHI clinical trials, observational studies have also reported an increased risk of breast cancer for estrogen plus progestin therapy and a smaller increased risk for estrogen-alone therapy, after several years of use. One large meta-analysis of prospective cohort studies reported increased risks that were dependent upon duration of use and could last up to > 10 years after discontinuation of estrogen plus progestin therapy and estrogen-alone therapy. Extension of the WHI trials also demonstrated increased breast cancer risk associated with estrogen plus progestin therapy. Observational studies also suggest that the risk of breast cancer was greater, and became apparent earlier, with estrogen plus progestin therapy as compared to estrogen-alone therapy. However, these studies have not found significant variation in the risk of breast cancer among different estrogen plus progestin combinations, doses, or routes of administration.

The use of estrogen-alone and estrogen plus progestin has been reported to result in an increase in abnormal mammograms requiring further evaluation.

All women should receive yearly breast examinations by a healthcare provider and perform monthly breast self-examinations. In addition, mammography examinations should be scheduled based on patient age, risk factors, and prior mammogram results.

c. Ovarian cancer

The WHI estrogen plus progestin substudy reported a statistically non-significant increased risk of ovarian cancer. After an average follow-up of 5.6 years, the relative risk for ovarian cancer for CE plus MPA versus placebo was 1.58 (95 percent CI, 0.77 – 3.24). The absolute risk for CE plus MPA versus placebo was 4 versus 3 cases per 10,000 women-years.

A meta-analysis of 17 prospective and 35 retrospective epidemiology studies found that women who used hormonal therapy for menopausal symptoms had an increased risk for ovarian cancer. The primary analysis, using case-control comparisons, included 12,110 cancer cases from the 17 prospective studies. The relative risks associated with current use of hormonal therapy was 1.41 (95% confidence interval [CI] 1.32 to 1.50); there was no difference in the risk estimates by duration of the exposure (less than 5 years [median of 3 years] vs. greater than 5 years [median of 10 years] of use before the cancer diagnosis). The relative risk associated with combined current and recent use (discontinued use within 5 years before cancer diagnosis) was 1.37 (95% CI 1.27–1.48), and the elevated risk was significant for both estrogen-alone and estrogen plus progestin products. The exact duration of hormone therapy use associated with an increased risk of ovarian cancer, however, is unknown.

3. Probable Dementia

In the WHIMS estrogen-alone ancillary study of WHI, a population of 2,947 hysterectomized women 65 to 79 years of age was randomized to daily CE (0.625 mg)-alone or placebo.

After an average follow-up of 5.2 years, 28 women in the estrogen-alone group and 19 women in the placebo group were diagnosed with probable dementia. The relative risk of probable dementia for CE-alone versus placebo was 1.49 (95 percent CI, 0.83–2.66). The absolute risk of probable dementia for CE-alone versus placebo was 37 versus 25 cases per 10,000 women-years. (See CLINICAL STUDIES and PRECAUTIONS, Geriatric Use.)

In the WHIMS estrogen plus progestin ancillary study of WHI, a population of 4,532 postmenopausal women 65 to 79 years of age was randomized to daily CE (0.625 mg) plus MPA (2.5 mg) or placebo.

After an average follow-up of 4 years, 40 women in the CE plus MPA group and 21 women in the placebo group were diagnosed with probable dementia. The relative risk of probable dementia for CE plus MPA versus placebo was 2.05 (95 percent CI 1.21–3.48). The absolute risk of probable dementia for CE plus MPA versus placebo was 45 versus 22 cases per 10,000 women-years. (See CLINICAL STUDIES and PRECAUTIONS, Geriatric Use.)

When data from the two populations in the WHIMS estrogen-alone and estrogen plus progestin ancillary studies were pooled as planned in the WHIMS protocol, the reported overall relative risk for probable dementia was 1.76 (95 percent CI, 1.19–2.60). Since both substudies were conducted in women 65 to 79 years of age, it is unknown whether these findings apply to younger postmenopausal women. (See PRECAUTIONS, Geriatric Use.)

4. Gallbladder Disease

A 2- to 4-fold increase in the risk of gallbladder disease requiring surgery in postmenopausal women receiving postmenopausal estrogens has been reported.

5. Hypercalcemia

Estrogen administration may lead to severe hypercalcemia in patients with breast cancer and bone metastases. If hypercalcemia occurs, use of the drug should be stopped and appropriate measures taken to reduce the serum calcium level.

6. Visual Abnormalities

Retinal vascular thrombosis has been reported in patients receiving estrogens. Discontinue medication pending examination if there is sudden partial or complete loss of vision, or a sudden onset of proptosis, diplopia, or migraine. If examination reveals papilledema or retinal vascular lesions, estrogens should be permanently discontinued.

7. Anaphylactic Reaction and Angioedema

Cases of anaphylaxis, which developed within minutes to hours after using PREMARIN Intravenous and require emergency medical management, have been reported in the postmarketing setting. Skin (hives, pruritis, swollen lips-tongue-face) and either respiratory tract (respiratory compromise) or gastrointestinal tract (abdominal pain, vomiting) involvement has been noted.

Angioedema involving the tongue, larynx, face, hands, and feet requiring medical intervention has occurred postmarketing in patients using PREMARIN Intravenous. If angioedema involves the tongue, glottis, or larynx, airway obstruction may occur. Patients who develop an anaphylactic reaction with or without angioedema after treatment with PREMARIN Intravenous should not receive PREMARIN Intravenous again.

8. Hereditary Angioedema

Exogenous estrogens may induce or exacerbate symptoms of angioedema, particularly in women with hereditary angioedema.

PRECAUTIONS

A. General

Premarin Intravenous for injection is indicated for short-term use. However, warnings, precautions and adverse reactions associated with oral Premarin treatment should be taken into account.

1. Addition of a progestin when a woman has not had a hysterectomy

Studies of the addition of a progestin for 10 or more days of a cycle of estrogen administration or daily with estrogen in a continuous regimen have reported a lowered incidence of endometrial hyperplasia than would be induced by estrogen treatment alone. Endometrial hyperplasia may be a precursor to endometrial cancer.

There are, however, possible risks which may be associated with the use of progestins with estrogens compared to estrogen-alone regimens. These include an increased risk of breast cancer.

2. Elevated blood pressure

In a small number of case reports, substantial increases in blood pressure have been attributed to idiosyncratic reactions to estrogens. In a large, randomized, placebo-controlled clinical trial, a generalized effect of estrogen therapy on blood pressure was not seen.

3. Hypertriglyceridemia

In women with pre-existing hypertriglyceridemia, estrogen therapy may be associated with elevations of plasma triglycerides leading to pancreatitis. Consider discontinuation of treatment if pancreatitis occurs.

4. Hepatic impairment and/or past history of cholestatic jaundice

Estrogens may be poorly metabolized in women with impaired liver function. For women with a history of cholestatic jaundice associated with past estrogen use or with pregnancy, caution should be exercised, and in the case of recurrence, medication should be discontinued.

5. Hypothyroidism

Estrogen administration leads to increased thyroid-binding globulin (TBG) levels. Women with normal thyroid function can compensate for the increased TBG by making more thyroid hormone, thus maintaining free T4 and T3 serum concentrations in the normal range. Women dependent on thyroid hormone replacement therapy who are also receiving estrogens may require increased doses of their thyroid replacement therapy. These women should have their thyroid function monitored in order to maintain their free thyroid hormone levels in an acceptable range.

6. Fluid retention

Estrogens may cause some degree of fluid retention. Women with conditions that might be influenced by this factor, such as a cardiac or renal dysfunction, warrant careful observation when estrogens are prescribed.

7. Hypocalcemia

Estrogen therapy should be used with caution in individuals with hypoparathyroidism as estrogen-induced hypocalcemia may occur.

8. Exacerbation of endometriosis

A few cases of malignant transformation of residual endometrial implants have been reported in women treated post-hysterectomy with estrogen-alone therapy. For women known to have residual endometriosis post-hysterectomy, the addition of progestin should be considered.

9. Exacerbation of other conditions

Estrogen therapy may cause an exacerbation of asthma, diabetes mellitus, epilepsy, migraine, porphyria, systemic lupus erythematosus, and hepatic hemangiomas and should be used with caution in women with these conditions.

B. Patient Information

Physicians are advised to discuss the contents of the PATIENT INFORMATION leaflet with patients who are being treated with Premarin Intravenous.

C. Laboratory Tests

Estrogen administration should be guided by clinical response at the lowest dose, rather than laboratory monitoring.

D. Drug-Laboratory Test Interactions

1. Accelerated prothrombin time, partial thromboplastin time, and platelet aggregation time; increased platelet count; increased factors II, VII antigen, VIII antigen, VIII coagulant activity, IX, X, XII, VII-X complex, II-VII-X complex, and beta-thromboglobulin; decreased levels of anti-factor Xa and antithrombin III, decreased antithrombin III activity; increased levels of fibrinogen and fibrinogen activity; increased plasminogen antigen and activity.
2. Increased thyroid-binding globulin (TBG) leading to increased circulating total thyroid hormone, as measured by protein-bound iodine (PBI), T4 levels (by column or by radioimmunoassay) or T3 levels by radioimmunoassay. T3 resin uptake is decreased, reflecting the elevated TBG. Free T4 and free T3 concentrations are unaltered. Patients on thyroid replacement therapy may require higher doses of thyroid hormone.
3. Other binding proteins may be elevated in serum, i.e., corticosteroid binding globulin (CBG), SHBG, leading to increased total circulating corticosteroids and sex steroids respectively. Free hormone concentrations, such as testosterone and estradiol, may be decreased. Other plasma proteins may be increased (angiotensinogen/renin substrate, alpha-1-antitrypsin, ceruloplasmin).
4. Increased plasma high-density lipoprotein (HDL) and HDL2 subfraction concentrations, reduced low-density lipoprotein (LDL) cholesterol concentration, increased triglyceride levels.
5. Impaired glucose tolerance.

E. Carcinogenesis, Mutagenesis, and Impairment of Fertility

(See BOXED WARNINGS, WARNINGS, and PRECAUTIONS.)

Long-term continuous administration of natural and synthetic estrogens in certain animal species increases the frequency of carcinomas of the breast, uterus, cervix, vagina, testis, and liver.

F. Pregnancy

Premarin Intravenous should not be used during pregnancy. (See CONTRAINDICATIONS.)

G. Nursing Mothers

Premarin Intravenous should not be used during lactation. Estrogen administration to nursing women has been shown to decrease the quantity and quality of the breast milk. Detectable amounts of estrogens have been identified in the breast milk of women receiving estrogens. Caution should be exercised when Premarin Intravenous is administered to a nursing woman.

H. Pediatric Use

Estrogen therapy has been used for the induction of puberty in adolescents with some forms of pubertal delay. Safety and effectiveness in pediatric patients have not otherwise been established.

Large and repeated doses of estrogen over an extended time period have been shown to accelerate epiphyseal closure, which could result in short adult stature if treatment is initiated before the completion of physiologic puberty in normally developing children. If estrogen is administered to patients whose bone growth is not complete, periodic monitoring of bone maturation and effects on epiphyseal centers is recommended during estrogen administration.

Estrogen treatment of prepubertal girls also induces premature breast development and vaginal cornification, and may induce vaginal bleeding. In boys, estrogen treatment may modify the normal pubertal process and induce gynecomastia.

I. Geriatric Use

There have not been sufficient numbers of geriatric patients involved in studies utilizing Premarin to determine whether those over 65 years of age differ from younger subjects in their response to Premarin.

The Women's Health Initiative Studies

In the WHI estrogen-alone substudy (daily CE [0.625 mg]-alone versus placebo), there was a higher relative risk of stroke in women greater than 65 years of age. (See CLINICAL STUDIES.)

In the WHI estrogen plus progestin substudy (daily CE [0.625 mg] plus MPA [2.5 mg] versus placebo), there was a higher relative risk of nonfatal stroke and invasive breast cancer in women greater than 65 years of age. (See CLINICAL STUDIES.)

The Women's Health Initiative Memory Study

In the WHIMS ancillary studies of postmenopausal women 65 to 79 years of age, there was an increased risk of developing probable dementia in women receiving estrogen-alone or estrogen plus progestin when compared to placebo. (See CLINICAL STUDIES and WARNINGS, Probable Dementia.)

Since both ancillary studies were conducted in women 65 to 79 years of age, it is unknown whether these findings apply to younger postmenopausal women. (See CLINICAL STUDIES and WARNINGS, Probable Dementia.)

ADVERSE REACTIONS

See BOXED WARNINGS, WARNINGS, and PRECAUTIONS.

Premarin Intravenous for injection is indicated for short-term use. However, the warnings, precautions and adverse reactions associated with oral Premarin treatment should be taken into account.

The following adverse reactions have been identified during post-approval use of oral or intravenous Premarin. Because these reactions are reported voluntarily from a population of uncertain size, it is not possible to reliably estimate their frequency or establish a causal relationship to drug exposure.

Genitourinary system

Abnormal uterine bleeding/spotting.
Dysmenorrhea or pelvic pain.
Increase in size of uterine leiomyomata.
Vaginitis, including vaginal candidiasis.
Change in amount of cervical secretion.
Change in cervical ectropion.
Ovarian cancer.
Endometrial hyperplasia.
Endometrial cancer.

Breasts

Tenderness, enlargement, pain, discharge, galactorrhea.
Fibrocystic breast changes.
Breast cancer.

Cardiovascular

Deep and superficial venous thrombosis.
Pulmonary embolism.
Thrombophlebitis.
Myocardial infarction.
Stroke.
Increase in blood pressure.

Gastrointestinal

Nausea, vomiting.
Abdominal cramps, bloating.
Cholestatic jaundice.
Increased incidence of gallbladder disease.
Pancreatitis.
Enlargement of hepatic hemangiomas.
Ischemic colitis.

Skin

Chloasma or melasma that may persist when drug is discontinued.
Erythema multiforme.
Erythema nodosum.
Hemorrhagic eruption.
Loss of scalp hair.
Hirsutism.
Pruritis.
Rash.

Eyes

Retinal vascular thrombosis.
Intolerance to contact lenses.

Central Nervous System

Headache.
Migraine.
Dizziness.
Mental depression.
Exacerbation of chorea.
Nervousness.
Exacerbation of epilepsy.
Dementia.
Possible growth potentiation of benign meningioma.

Miscellaneous

Increase or decrease in weight.
Glucose intolerance.
Aggravation of porphyria.
Edema.
Arthralgia.
Leg cramps.
Changes in libido.
Urticaria.
Hypocalcemia (preexisting condition).
Injection site pain.
Injection site edema.
Phlebitis (injection site).
Exacerbation of asthma.
Increased triglycerides.

OVERDOSAGE

Overdosage of estrogen may cause nausea, vomiting, breast tenderness, abdominal pain, drowsiness and fatigue, and withdrawal bleeding may occur in women. Treatment of overdose consists of discontinuation of Premarin therapy with institution of appropriate symptomatic care.

DOSAGE AND ADMINISTRATION

For treatment of abnormal uterine bleeding due to hormonal imbalance in the absence of organic pathology:

One 25 mg injection, intravenously or intramuscularly. Intravenous use is preferred since more rapid response can be expected from this mode of administration. Repeat in 6 to 12 hours if necessary. The use of Premarin Intravenous for injection does not preclude the advisability of other appropriate measures.

One should adhere to the usual precautionary measures governing intravenous administration. Injection should be made SLOWLY to obviate the occurrence of flushes.

Infusion of Premarin Intravenous for injection with other agents is not generally recommended. In emergencies, however, when an infusion has already been started it may be expedient to make the injection into the tubing just distal to the infusion needle. If so used, compatibility of solutions must be considered.

COMPATIBILITY OF SOLUTIONS

Premarin Intravenous is compatible with normal saline, dextrose, and invert sugar solutions. It is not compatible with protein hydrolysate, ascorbic acid, or any solution with an acid pH.

DIRECTIONS FOR STORAGE AND RECONSTITUTION

STORAGE BEFORE RECONSTITUTION

Store package in refrigerator, 2° to 8°C (36° to 46°F).

TO RECONSTITUTE

Reconstitute Premarin Intravenous with 5 mL of Sterile Water for Injection, USP. Introduce the sterile diluent slowly against the side of the vial and agitate gently. Do not shake violently. Use immediately after reconstitution.

HOW SUPPLIED

NDC 0046-0749-05–Each package provides one single-dose vial containing 25 mg/vial of conjugated estrogens, USP, for injection (also lactose 200 mg, sodium citrate 12.2 mg, and simethicone 0.2 mg). The pH is adjusted with sodium hydroxide or hydrochloric acid.

Premarin Intravenous (conjugated estrogens, USP) for injection is prepared by cryodesiccation.

PATIENT INFORMATION

Premarin Intravenous (conjugated estrogens, USP) for injection

Read this PATIENT INFORMATION which describes the benefit and major risks of your treatment, as well as how and when treatment should be used. This information does not take the place of talking to your healthcare provider about your medical condition or your treatment.

What is the most important information I should know about Premarin Intravenous (an estrogen mixture)?

- Using estrogen-alone increases your chance of getting cancer of the uterus (womb)
  Report any unusual vaginal bleeding right away. Vaginal bleeding after menopause may be a warning sign of cancer of the uterus (womb). Your healthcare provider should check any unusual vaginal bleeding to find out the cause.
- Do not use estrogen-alone to prevent heart disease, heart attacks, strokes, or dementia (decline in brain function)
- Using estrogen-alone may increase your chances of getting stroke or blood clots
- Using estrogen-alone may increase your chance of getting dementia, based on a study of women 65 years of age or older
- Do not use estrogens with progestins to prevent heart disease, heart attacks, strokes or dementia
- Using estrogens with progestins may increase your chances of getting heart attacks, strokes, breast cancer, or blood clots
- Using estrogens with progestins may increase your chance of getting dementia, based on a study of women 65 years of age or older
- You and your healthcare provider should talk regularly about whether you still need treatment with estrogens

What is Premarin Intravenous?

Premarin Intravenous is a medicine that contains a mixture of estrogen hormones.

Premarin Intravenous is used to:

- Treat certain types of abnormal uterine bleeding due to hormonal imbalance when your doctor has found no other cause of bleeding

Who should not use Premarin Intravenous?

Premarin Intravenous should not be used if you:

- Have unusual vaginal bleeding that has not been evaluated by your healthcare provider
- Currently have or have had certain cancers
  Estrogens may increase the chance of getting certain types of cancers, including cancer of the breast or uterus. If you have or have had cancer, talk with your healthcare provider about whether you should use Premarin Intravenous.
- Had a stroke or heart attack
- Currently have or have had blood clots
- Currently have or have had liver problems
- Have been diagnosed with a bleeding disorder
- Are allergic to Premarin Intravenous or any of its ingredients
  See the list of ingredients in Premarin Intravenous at the end of this leaflet.
- Think you may be pregnant

Tell your healthcare provider:

- If you are breast feeding
The hormones in Premarin Intravenous can pass into your breast milk.
- About all of your medical problems
Your healthcare provider may need to check you more carefully if you have certain conditions, such as asthma (wheezing), epilepsy (seizures), diabetes, migraine, endometriosis, lupus, problems with your heart, liver, thyroid, kidneys, or have high calcium levels in your blood.
- About all the medicines you take
This includes prescription and nonprescription medicines, vitamins, and herbal supplements. Some medicines may affect how Premarin Intravenous works.

What are the possible side effects of Premarin Intravenous?

Premarin Intravenous is for short-term use only. However, the risks associated with oral Premarin treatment should be taken into account.

Side effects are grouped by how serious they are and how often they happen when you are treated.

Serious, but less common side effects include:

- Heart attack
- Stroke
- Blood clots
- Dementia
- Breast cancer
- Cancer of the lining of the uterus (womb)
- Cancer of the ovary
- High blood pressure
- High blood sugar
- Gallbladder disease
- Liver problems
- Enlargement of benign tumors of the uterus ("fibroids")
- Severe allergic reactions

Call your healthcare provider right away if you get any of the following warning signs or any other unusual symptoms that concern you:

- New breast lumps
- Unusual vaginal bleeding
- Changes in vision or speech
- Sudden new severe headaches
- Severe pains in your chest or legs with or without shortness of breath, weakness and fatigue
- Swollen lips, tongue and face

Less serious, but common side effects include:

- Headache
- Breast pain
- Irregular vaginal bleeding or spotting
- Stomach or abdominal cramps, bloating
- Nausea and vomiting
- Hair loss
- Fluid retention
- Vaginal yeast infection

These are not all the possible side effects of Premarin. For more information, ask your healthcare provider or pharmacist for advice about side effects. You may report side effects to FDA at 1-800-FDA-1088.

What can I do to lower my chances of getting a serious side effect with Premarin Intravenous?

- If you have high blood pressure, high cholesterol (fat in the blood), diabetes, are overweight, or if you use tobacco, you may have higher chances for getting heart disease
  Ask your healthcare provider for ways to lower your chances for getting heart disease.

General information about the safe and effective use of Premarin Intravenous

Medicines are sometimes prescribed for conditions that are not mentioned in patient information leaflets. Do not use Premarin Intravenous for conditions for which it was not prescribed. Do not give Premarin Intravenous to other people, even if they have the same symptoms you have. It may harm them. Keep Premarin Intravenous out of the reach of children.

This leaflet provides a summary of the most important information about Premarin Intravenous. If you would like more information, talk with your healthcare provider or pharmacist. You can ask for information about Premarin Intravenous that is written for health professionals. To report SUSPECTED ADVERSE REACTIONS, contact Pfizer at 1-800-438-1985 or FDA at 1-800-FDA-1088 or www.fda.gov/medwatch.

What are the ingredients in Premarin IV?

Premarin Intravenous for injection contains a mixture of conjugated estrogens, which are a mixture of sodium estrone sulfate and sodium equilin sulfate and other components including sodium sulfate conjugates: 17α-dihydroequilin, 17α-estradiol, and 17β-dihydroequilin. Premarin Intravenous for injection also contains lactose, sodium citrate, simethicone, and sodium hydroxide or hydrochloric acid in dry form. The reconstituted solution is suitable for intravenous or intramuscular injection.

Each Premarin Intravenous (conjugated estrogens, USP) for injection package provides 25 mg/vial of conjugated estrogens, USP, in dry form for intravenous or intramuscular use.

This product's label may have been updated. For current full prescribing information, please visit www.pfizer.com.

LAB-0505-6.0
Revised 02/2024

PATIENT INFORMATION

Premarin
Intravenous
(conjugated estrogens, USP) for injection

Rx only

Read this PATIENT INFORMATION which describes the benefit and major risks of your treatment, as well as how and when treatment should be used. This information does not take the place of talking to your healthcare provider about your medical condition or your treatment.

What is the most important information I should know about Premarin Intravenous (an estrogen mixture)?

- Using estrogen-alone increases your chance of getting cancer of the uterus (womb)
  Report any unusual vaginal bleeding right away. Vaginal bleeding after menopause may be a warning sign of cancer of the uterus (womb). Your healthcare provider should check any unusual vaginal bleeding to find out the cause.
- Do not use estrogen-alone to prevent heart disease, heart attacks, strokes, or dementia (decline in brain function)
- Using estrogen-alone may increase your chances of getting stroke or blood clots
- Using estrogen-alone may increase your chance of getting dementia, based on a study of women 65 years of age or older
- Do not use estrogens with progestins to prevent heart disease, heart attacks, strokes or dementia
- Using estrogens with progestins may increase your chances of getting heart attacks, strokes, breast cancer, or blood clots
- Using estrogens with progestins may increase your chance of getting dementia, based on a study of women 65 years of age or older
- You and your healthcare provider should talk regularly about whether you still need treatment with estrogens.

What is Premarin Intravenous?

Premarin Intravenous is a medicine that contains a mixture of estrogen hormones.

Premarin Intravenous is used to:

- Treat certain types of abnormal uterine bleeding due to hormonal imbalance when your doctor has found no other cause of bleeding

Who should not use Premarin Intravenous?

Premarin Intravenous should not be used if you:

- Have unusual vaginal bleeding that has not been evaluated by your healthcare provider
- Currently have or have had certain cancers
  Estrogens may increase the chance of getting certain types of cancers, including cancer of the breast or uterus. If you have or have had cancer, talk with your healthcare provider about whether you should use Premarin Intravenous.
- Had a stroke or heart attack
- Currently have or have had blood clots
- Currently have or have had liver problems
- Have been diagnosed with a bleeding disorder
- Are allergic to Premarin Intravenous or any of its ingredients
  See the list of ingredients in Premarin Intravenous at the end of this leaflet.
- Think you may be pregnant

Tell your healthcare provider:

- If you are breast feeding
The hormones in Premarin Intravenous can pass into your breast milk.
- About all of your medical problems
Your healthcare provider may need to check you more carefully if you have certain conditions, such as asthma (wheezing), epilepsy (seizures), diabetes, migraine, endometriosis, lupus, problems with your heart, liver, thyroid, kidneys, or have high calcium levels in your blood.
- About all the medicines you take
This includes prescription and nonprescription medicines, vitamins, and herbal supplements. Some medicines may affect how Premarin Intravenous works.

What are the possible side effects of Premarin Intravenous?

Premarin Intravenous is for short-term use only. However, the risks associated with oral Premarin treatment should be taken into account.

Side effects are grouped by how serious they are and how often they happen when you are treated.

Serious, but less common side effects include:

- Heart attack
- Stroke
- Blood clots
- Dementia
- Breast cancer
- Cancer of the lining of the uterus (womb)
- Cancer of the ovary
- High blood pressure
- High blood sugar
- Gallbladder disease
- Liver problems
- Enlargement of benign tumors of the uterus ("fibroids")
- Severe allergic reactions

Call your healthcare provider right away if you get any of the following warning signs or any other unusual symptoms that concern you:

- New breast lumps
- Unusual vaginal bleeding
- Changes in vision or speech
- Sudden new severe headaches
- Severe pains in your chest or legs with or without shortness of breath, weakness and fatigue
- Swollen lips, tongue and face

Less serious, but common side effects include:

- Headache
- Breast pain
- Irregular vaginal bleeding or spotting
- Stomach or abdominal cramps, bloating
- Nausea and vomiting
- Hair loss
- Fluid retention
- Vaginal yeast infection

These are not all the possible side effects of Premarin. For more information, ask your healthcare provider or pharmacist for advice about side effects. You may report side effects to FDA at 1-800-FDA-1088.

What can I do to lower my chances of getting a serious side effect with Premarin Intravenous?

- If you have high blood pressure, high cholesterol (fat in the blood), diabetes, are overweight, or if you use tobacco, you may have higher chances for getting heart disease
  Ask your healthcare provider for ways to lower your chances for getting heart disease.

General information about the safe and effective use of Premarin Intravenous

Medicines are sometimes prescribed for conditions that are not mentioned in patient information leaflets. Do not use Premarin Intravenous for conditions for which it was not prescribed. Do not give Premarin Intravenous to other people, even if they have the same symptoms you have. It may harm them. Keep Premarin Intravenous out of the reach of children.

This leaflet provides a summary of the most important information about Premarin Intravenous. If you would like more information, talk with your healthcare provider or pharmacist. You can ask for information about Premarin Intravenous that is written for health professionals. To report SUSPECTED ADVERSE REACTIONS, contact Pfizer at 1-800-438-1985 or FDA at 1-800-FDA-1088 or www.fda.gov/medwatch.

What are the ingredients in Premarin IV?

Premarin Intravenous for injection contains a mixture of conjugated estrogens, which are a mixture of sodium estrone sulfate and sodium equilin sulfate and other components including sodium sulfate conjugates: 17α-dihydroequilin, 17α-estradiol, and 17β-dihydroequilin. Premarin Intravenous for injection also contains lactose, sodium citrate, simethicone, and sodium hydroxide or hydrochloric acid in dry form. The reconstituted solution is suitable for intravenous or intramuscular injection.

Each Premarin Intravenous (conjugated estrogens, USP) for injection package provides 25 mg/vial of conjugated estrogens, USP, in dry form for intravenous or intramuscular use.

This product's label may have been updated. For current full prescribing information, please visit www.pfizer.com

LAB-0518-4.0
Rev 12/2021

PRINCIPAL DISPLAY PANEL - 25 mg Vial Label

Single-dose vial

Refrigerate at 2° to 8°C (36° to 46°F).

NDC 0046-0749-05
Rx only

Pfizer

Premarin® Intravenous
(conjugated estrogens, USP) for injection
Prepared by cryodesiccation.

25 mg/vial

To be reconstituted with Sterile Water for Injection, USP.
See package circular for reconstitution
instructions and complete directions for use.
Distributed by Wyeth Pharmaceuticals LLC
A subsidiary of Pfizer Inc.

222890
cod. 39

PRINCIPAL DISPLAY PANEL - 25 mg Vial Carton

Pfizer
NDC 0046-0749-05
Rx only

Premarin® Intravenous
(conjugated estrogens,
USP) for injection

25 mg/vial

Prepared by cryodesiccation.

This package provides one
single-dose vial containing
25 mg/vial of conjugated estrogens,
USP, for injection.